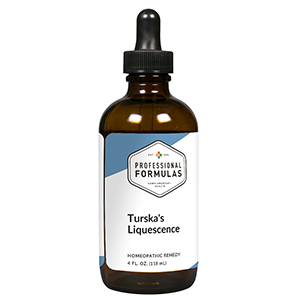 DRUG LABEL: Turskas Liquescence
NDC: 63083-3008 | Form: LIQUID
Manufacturer: Professional Complementary Health Formulas
Category: homeopathic | Type: HUMAN OTC DRUG LABEL
Date: 20190815

ACTIVE INGREDIENTS: ACONITUM NAPELLUS WHOLE 3 [hp_X]/118 mL; BRYONIA ALBA ROOT 3 [hp_X]/118 mL; GELSEMIUM SEMPERVIRENS ROOT 3 [hp_X]/118 mL; PHYTOLACCA AMERICANA ROOT 4 [hp_X]/118 mL
INACTIVE INGREDIENTS: ALCOHOL; WATER

T8

ACTIVE INGREDIENTS

Aconitum napellus 3X
Bryonia 3X
Gelsemium sempervirens 3X
Phytolacca decandra 4X

QUESTIONS

Professional Formulas

PO Box 2034 Lake Oswego, OR 97035

INDICATIONS

Temporarily relieves minor aches, pains, soreness, or inflammation due to overexertion, fatigue, or illness.*

PURPOSE

*Claims based on traditional homeopathic practice, not accepted medical evidence. Not FDA evaluated.

WARNINGS

In case of overdose, get medical help or contact a poison control center right away.

Keep out of the reach of children.

PREGNANCY OR BREAST FEEDING

If pregnant or breastfeeding, ask a healthcare professional before use.

DIRECTIONS

Place drops under tongue 30 minutes before/after meals. Adults and children 12 years and over: Take one full dropper up to 2 times per day. For immediate onset of symptoms, take 10 to 15 drops every 15 minutes up to 3 hours. For less severe symptoms, take 10-15 drops hourly up to 8 hours. Consult a physician for use in children under 12 years of age.

OTHER INFORMATION

Tamper resistant. If seal is broken, do not use. After opening, close container tightly and store at room temperature away from heat.

INACTIVE INGREDIENTS

20% ethanol, purified water.

LABEL

Est 1985

Professional Formulas

Complementary Health

Turskas Liquescence

Homeopathic Remedy

4 FL. OZ. (118 mL)